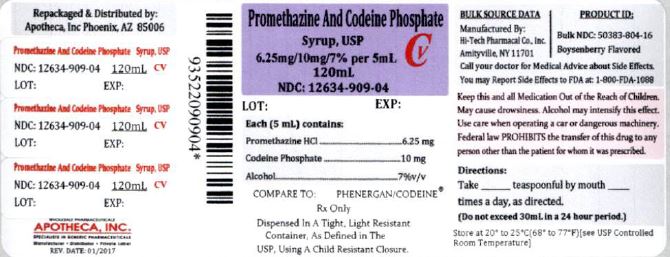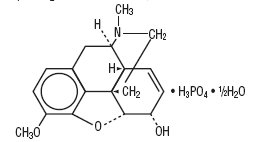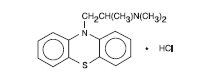 DRUG LABEL: Promethazine Hydrochloride and Codeine Phosphate
NDC: 12634-909 | Form: SYRUP
Manufacturer: Apotheca Inc
Category: prescription | Type: HUMAN PRESCRIPTION DRUG LABEL
Date: 20170303
DEA Schedule: CV

ACTIVE INGREDIENTS: CODEINE PHOSPHATE 10 mg/5 mL; PROMETHAZINE HYDROCHLORIDE 6.25 mg/5 mL
INACTIVE INGREDIENTS: ALCOHOL; ASCORBIC ACID; ANHYDROUS CITRIC ACID; D&C RED NO. 33; FD&C BLUE NO. 1; FD&C YELLOW NO. 6; METHYLPARABEN; PROPYLENE GLYCOL; PROPYLPARABEN; WATER; SACCHARIN SODIUM; SODIUM BENZOATE; TRISODIUM CITRATE DIHYDRATE; SUCROSE

PROMETHAZINE HYDROCHLORIDE AND CODEINE PHOSPHATE SYRUP

BOXED WARNING

WARNING: Respiratory Depression in Children and Death Related to

Ultra-Rapid Metabolism of Codeine to Morphine

Respiratory Depression in Children

The combination of promethazine hydrochloride and codeine phosphate iscontraindicated in pediatric patients less than 6 years of age. Concomitantadministration of promethazine products with other respiratory depressantshas an association with respiratory depression, and sometimes death, inpediatric patients.

Postmarketing cases of respiratory depression, including fatalities, havebeen reported with use of promethazine hydrochloride in pediatric patientsless than 2 years of age. A wide range of weight-based doses ofpromethazine hydrochloride have resulted in respiratory depression inthese patients.

Death Related to Ultra-Rapid Metabolism of Codeine to Morphine

Respiratory depression and death have occurred in children who receivedcodeine following tonsillectomy and/or adenoidectomy and had evidenceof being ultra-rapid metabolizers of codeine due to a CYP2D6 polymorphism.

DESCRIPTION

Each 5 mL (one teaspoonful), for oral administration contains: Promethazine hydrochloride 6.25 mg; codeine phosphate 10 mg. Alcohol 7%.

Inactive Ingredients: Artificial boysenberry flavor, ascorbic acid, citric acid, D&C Red No. 33, FD&C Blue No. 1, FD&C Yellow No. 6, methylparaben, propylene glycol, propylparaben, purified water, saccharin sodium, sodium benzoate, sodium citrate, and sucrose syrup.

Codeine is one of the naturally occurring phenanthrene alkaloids of opium derived from the nopium poppy; it is classified pharmacologically as a narcotic analgesic. Codeine phosphate may be chemically designated as 7,8-Didehydro-4, 5α-epoxy- 3-methoxy-17-methylmorphinan-6α-ol phosphate (1:1)(salt) hemihydrate.

The phosphate salt of codeine occurs as white, needle-shaped crystals or white crystalline powder. Codeine phosphate is freely soluble in water and slightly soluble in alcohol. It has a molecular weight of 406.37, a molecular formula of C18H21NO3 H3PO4 • ½ H20, and the following structural formula:

Promethazine hydrochloride, a phenothiazine derivative, is chemically designated as (±)-10-[2-(Dimethylamino)propyl] phenothiazine monohydrochloride.

Promethazine hydrochloride occurs as a white to faint yellow, practically odorless, crystalline powder which slowly oxidizes and turns blue on prolonged exposure to air. It is soluble in water and freely soluble in alcohol. It has a molecular weight of 320.88, a molecular formula of C17H20N2S•HCl, and the following structural formula:

CLINICAL PHARMACOLOGY

Codeine: Narcotic analgesics, including codeine, exert their primary effects on the central nervous system and gastrointestinal tract. The analgesic effects of codeine are due to its central action; however, the precise sites of action have not been determined, and the mechanisms involved appear to be quite complex. Codeine resembles morphine both structurally and pharmacologically, but its actions at the doses of codeine used therapeutically are milder, with less sedation, respiratory depression, and gastrointestinal, urinary, and pupillary effects. Codeine produces an increase in biliary tract pressure, but less than morphine or meperidine. Codeine is less constipating than morphine.

Codeine has good antitussive activity, although less than that of morphine at equal doses. It is used in preference to morphine, because side effects are infrequent at the usual antitussive dose of codeine.

Codeine in oral therapeutic dosage does not usually exert major effects on the cardiovascular system.

Narcotic analgesics may cause nausea and vomiting by stimulating the chemoreceptor trigger zone (CTZ); however, they also depress the vomiting center, so that subsequent doses are unlikely to produce vomiting. Nausea is minimal after usual oral doses of codeine.

Narcotic analgesics cause histamine release, which appears to be responsible for wheals or urticaria sometimes seen at the site of injection on parenteral administration. Histamine release may also produce dilation of cutaneous blood vessels, with resultant flushing of the face and neck, pruritus, and sweating.

Codeine and its salts are well absorbed following both oral and parenteral administration. Codeine is about 2/3 as effective orally as parenterally. Codeine is metabolized primarily in the liver by enzymes of the endoplasmic reticulum, where it undergoes 0-demethylation, N-demethylation, and partial conjugation with glucuronic acid. The drug is excreted primarily in the urine, largely as inactive metabolites and small amounts of free and conjugated morphine. Negligible amounts of codeine and its metabolites are found in the feces.

Following oral or subcutaneous administration of codeine, the onset of analgesia occurs within 15 to 30 minutes and lasts for four to six hours.

The cough-depressing action, in animal studies, was observed to occur 15 minutes after oral administration of codeine, peak action at 45 to 60 minutes after ingestion. The duration of action, which is dose-dependent, usually did not exceed 3 hours.

Promethazine: Promethazine is a phenothiazine derivative which differs structurally from the antipsychotic phenothiazines by the presence of a branched side chain and no ring substitution. It is thought that this configuration is responsible for its relative lack (1/10 that of chlorpromazine) of dopamine antagonist properties.

Promethazine is an H1 receptor blocking agent. In addition to its antihistaminic action, it provides clinically useful sedative and antiemetic effects.

Promethazine is well absorbed from the gastrointestinal tract. Clinical effects are apparent within 20 minutes after oral administration and generally last four to six hours, although they may persist as long as 12 hours. Promethazine is metabolized by the liver to a variety of compounds; the sulfoxides of promethazine and N-demethylpromethazine are the predominant metabolites appearing in the urine.

INDICATIONS AND USAGE

Promethazine hydrochloride and codeine phosphate syrup is indicated for the temporary relief of coughs and upper respiratory symptoms associated with allergy or the common cold.

CONTRAINDICATIONS

The combination of promethazine hydrochloride and codeine phosphate is contraindicated in pediatric patients less than 6 years of age, because the combination may cause fatal respiratory depression in this age population.

Codeine sulfate is contraindicated for postoperative pain management in children who have undergone tonsillectomy and/or adenoidectomy.

Codeine is contraindicated in patients with a known hypersensitivity to the drug.

Promethazine is contraindicated in comatose states, and in individuals known to be hypersensitive or to have had an idiosyncratic reaction to promethazine or to other phenothiazines.

Antihistamines and codeine are both contraindicated for use in the treatment of lower respiratory tract symptoms, including asthma.

WARNINGS

Respiratory Depression in Children

The combination of promethazine hydrochloride and codeine phosphate is contraindicated in pediatric patients less than 6 years of age. Concomitant administration of promethazine products with other respiratory depressants has an association with respiratory depression, and sometimes death, in pediatric patients.

Postmarketing cases of respiratory depression, including fatalities, have been reported with use of promethazine hydrochloride in pediatric patients less than 2 years of age. A wide range of weight-based doses of promethazine hydrochloride have resulted in respiratory depression in these patients.

Respiratory depression leading to arrest, coma, and death has occurred with the use of codeine antitussives in young children, particularly in the under-one-year infants whose ability to deactivate the drug is not fully developed.

Codeine

Death Related to Ultra-Rapid Metabolism of Codeine to Morphine

Respiratory depression and death have occurred in children who received codeine in the post-operative period following tonsillectomy and/or adenoidectomy and had evidence of being ultra-rapid metabolizers of codeine (i.e., multiple copies of the gene for cytochrome P450 isoenzyme 2D6 or high morphine concentrations). Deaths have also occurred in nursing infants who were exposed to high levels of morphine in breast milk because their mothers were ultra-rapid metabolizers of codeine. (See PRECAUTIONS – Nursing Mothers

Some individuals may be ultra-rapid metabolizers because of a specific CYP2D6 genotype (gene duplications denoted as *1/*1xN or *1/*2xN). The prevalence of this CYP2D6 phenotype varies widely and has been estimated at 0.5 to 1% in Chinese and Japanese, 0.5 to 1% in Hispanics, 1 to 10% in Caucasians, 3% in African Americans and 16 to 28% in North Africans, Ethiopians, and Arabs. Data are not available for other ethnic groups. These individuals convert codeine into its active metabolite, morphine, more rapidly and completely than other people. This rapid conversion-results in higher than expected serum morphine levels. Even at labeled dosage regimens, individuals who are ultra-rapid metabolizers may have life-threatening or fatal respiratory depression or experience signs of overdose (such as extreme sleepiness, confusion, or shallow breathing). (See OVERDOSAGE).

Children with obstructive sleep apnea who are treated with codeine for post-tonsillectomy and/or adenoidectomy pain may be particularly sensitive to the respiratory depressant effects of codeine that has been rapidly metabolized to morphine. Codeine is contraindicated for post-operative pain management in all pediatric patients undergoing tonsillectomy and/or adenoidectomy. (See CONTRAINDICATIONS).

When prescribing codeine-containing drugs, healthcare providers should choose the lowest effective dose for the shortest period of time and inform patients and caregivers about these risks and the signs of morphine overdose.

Codeine: Dosage of codeine SHOULD NOT BE INCREASED if cough fails to respond; an unresponsive cough should be reevaluated in 5 days or sooner for possible underlying pathology, such as foreign body or lower respiratory tract disease.

Codeine may cause or aggravate constipation.

Administration of codeine may be accompanied by histamine release and should be used with caution in atopic children.

Head Injury And Increased Intracranial Pressure: The respiratory- depressant effects of narcotic analgesics and their capacity to elevate cerebrospinal fluid pressure may be markedly exaggerated in the presence of head injury, intracranial lesions or a preexisting increase in intracranial pressure. Narcotics may produce adverse reactions which may obscure the clinical course of patients with head injuries.

Asthma And Other Respiratory Conditions: Narcotic analgesics or cough suppressants, including codeine, should not be used in asthmatic patients (see CONTRAINDICATIONS). Nor should they be used in acute febrile illness associated with productive cough or in chronic respiratory disease where interference with ability to clear the tracheobronchial tree of secretions would have a deleterious effect on the patient’s respiratory function.

Hypotensive Effect: Codeine may produce orthostatic hypotension in ambulatory patients.

Promethazine:

CNS Depression – Promethazine may impair the mental and/or physical abilities required for the performance of potentially hazardous tasks, such as driving a vehicle or operating machinery. The impairment may be amplified by concomitant use of other central-nervous-system depressants such as alcohol, sedatives/hypnotics (including barbiturates), narcotics, narcotic analgesics, general anesthetics, tricyclic antidepressants, and tranquilizers; therefore such agents should either be eliminated or given in reduced dosage in the presence of promethazine HCl (see PRECAUTIONS- Information for Patients and Drug Interactions).

Respiratory Depression – Promethazine may lead to potentially fatal respiratory depression.

Use of Promethazine in patients with compromised respiratory function (e.g., COPD, sleep apnea) should be avoided.

Lower Seizure Threshold – Promethazine may lower seizure threshold. It should be used with caution in persons with seizure disorders or in persons who are using concomitant medications, such as narcotics or local anesthetics, which may also affect seizure threshold.

Bone-Marrow Depression – Promethazine should be used with caution in patients with bone-marrow depression. Leukopenia and agranulocytosis have been reported, usually when promethazine HCl has been used in association with other known marrow-toxic agents.

Neuroleptic Malignant Syndrome – A potentially fatal symptom complex sometimes referred to as Neuroleptic Malignant Syndrome (NMS) has been reported in association with promethazine HCl alone or in combination with antipsychotic drugs. Clinical manifestations of NMS are hyperpyrexia, muscle rigidity, altered mental status and evidence of autonomic instability (irregular pulse or blood pressure, tachycardia, diaphoresis and cardiac dysrhythmias).

The diagnostic evaluation of patients with this syndrome is complicated. In arriving at a diagnosis, it is important to identify cases where the clinical presentation includes both serious medical illness (e.g., pneumonia, systemic infection, etc.) and untreated or inadequately treated extrapyramidal signs and symptoms (EPS). Other important considerations in the differential diagnosis include central anticholinergic toxicity, heat stroke, drug fever and primary central nervous system (CNS) pathology.

The management of NMS should include 1) immediate discontinuation of promethazine HCl, antipsychotic drugs, if any, and other drugs not essential to concurrent therapy, 2) intensive symptomatic treatment and medical monitoring, and 3) treatment of any concomitant serious medical problems for which specific treatments are available. There is no general agreement about specific pharmacological treatment regimens for uncomplicated NMS.

Since recurrences of NMS have been reported with phenothiazines, the reintroduction of promethazine HCl should be carefully considered.

Use in Pediatric Patients

THE COMBINATION OF PROMETHAZINE HYDROCHLORIDE AND CODEINE PHOSPHATE IS CONTRAINDICATED IN PEDIATRIC PATIENTS LESS THAN 6 YEARS OF AGE. CONCOMITANT ADMINISTRATION OF PROMETHAZINE PRODUCTS WITH OTHER RESPIRATORY DEPRESSANTS HAS AN ASSOCIATION WITH RESPIRATORY DEPRESSION, AND SOMETIMES DEATH, IN PEDIATRIC PATIENTS. THE ASSOCIATION DOES NOT DIRECTLY RELATE TO INDIVIDUALIZED WEIGHT-BASED DOSING, WHICH MIGHT OTHERWISE PERMIT SAFE ADMINISTRATION.

Respiratory depression and death have occurred in children with obstructive sleep apnea who received codeine in the post-operative period following tonsillectomy and/or adenoidectomy and had evidence of being ultra-rapid metabolizers of codeine (i.e., multiple copies of the gene for cytochrome P450 isoenzyme CYP2D6 or high morphine concentrations). These children may be particularly sensitive to the respiratory depressant effects of codeine that has been rapidly metabolized to morphine. Codeine is contraindicated for post-operative pain management in these patients (see WARNINGS – Death Related to Ultra-Rapid Metabolism of Codeine to Morphine and CONTRAINDICATIONS).

Excessively large dosages of antihistamines, including promethazine hydrochloride, in pediatric patients may cause sudden death (see OVERDOSAGE). Hallucinations and convulsions have occurred with therapeutic doses and overdoses of promethazine hydrochloride in pediatric patients. In pediatric patients who are acutely ill associated with dehydration, there is an increased susceptibility to dystonias with the use of promethazine HCl.

Other Considerations

Administration of promethazine has been associated with reported cholestatic jaundice.

PRECAUTIONS

Animal reproduction studies have not been conducted with the drug combination – promethazine and codeine. It is not known whether this drug combination can cause fetal harm when administered to a pregnant woman or can affect reproduction capacity. Promethazine hydrochloride and codeine phosphate should be given to a pregnant woman only if clearly needed.

General

Narcotic analgesics, including codeine, should be administered with caution and the initial dose reduced in patients with acute abdominal conditions, convulsive disorders, significant hepatic or renal impairment, fever, hypothyroidism, Addison’s disease, ulcerative colitis, prostatic hypertrophy, in patients with recent gastrointestinal or urinary tract surgery, and in the very young or elderly or debilitated patients.

Drugs having anticholinergic properties should be used with caution in patients with narrow-angle glaucoma, prostatic hypertrophy, stenosing peptic ulcer, pyloroduodenal obstruction, and bladder-neck obstruction.

Promethazine should be used cautiously in persons with cardiovascular disease or with impairment of liver function.

Information for Patients

Patients should be advised to measure Promethazine with Codeine Oral Solution with an accurate measuring device. A household teaspoon is not an accurate measuring device and could lead to overdosage, especially when a half a teaspoon is measured. A pharmacist can recommend an appropriate measuring device and can provide instructions for measuring the correct dose.

Promethazine and codeine may cause marked drowsiness or may impair the mental and/or physical abilities required for the performance of potentially hazardous tasks, such as driving a vehicle or operating machinery. Ambulatory patients should be told to avoid engaging in such activities until it is known that they do not become drowsy or dizzy from promethazine and codeine therapy. Pediatric patients should be supervised to avoid potential harm in bike riding or in other hazardous activities.

The concomitant use of alcohol or other central-nervous-system depressants, such as sedatives/hypnotics (including barbiturates), narcotics, narcotic analgesics, general anesthetics, tricyclic antidepressants, and tranquilizers may enhance impairment and should be avoided or their dosage reduced (see WARNINGS – CNS Depression and PRECAUTIONS – Drug Interactions).Patients should be advised to report any involuntary muscle movements.

Avoid prolonged exposure to the sun.

Codeine, like other narcotic analgesics, may produce orthostatic hypotension in some ambulatory patients. Patients should be cautioned accordingly.

Advise patients that some people have a genetic variation that results in codeine changing into morphine more rapidly and completely than other people. Most people are unaware of whether they are an ultra-rapid codeine metabolizer or not. These higher-than-normal levels of morphine in the blood may lead to life-threatening or fatal respiratory depression or signs of overdose such as extreme sleepiness, confusion, or shallow breathing. Children with this genetic variation who were prescribed codeine after tonsillectomy and/or adenoidectomy for obstructive sleep apnea may be at greatest risk based on reports of several deaths in this population due to respiratory depression. As a result, codeine is contraindicated in all children who undergo tonsillectomy and/or adenoidectomy. Advise caregivers of children receiving codeine for other reasons to monitor for signs of respiratory depression.

Nursing mothers taking codeine can also have higher morphine levels in their breast milk if they are ultra-rapid metabolizers. These higher levels of morphine in breast milk may lead to life-threatening or fatal side effects in nursing babies. Instruct nursing mothers to watch for signs of morphine toxicity in their infants including increased sleepiness (more than usual), difficulty breastfeeding, breathing difficulties, or limpness. Instruct nursing mothers to talk to the baby’s doctor immediately if they notice these signs and, if they cannot reach the doctor right away, to take the baby to an emergency room or call 911 (or local emergency services).

Drug Interactions

Codeine:

In patients receiving MAO inhibitors, an initial small test dose is advisable to allow observation of any excessive narcotic effects or MAOI interaction.

Promethazine:

CNS depressants – Promethazine may increase, prolong, or intensify the sedative action of other central-nervous-system depressants, such as alcohol, sedatives/hypnotics (including barbiturates), narcotics, narcotic analgesics, general anesthetics, tricyclic antidepressants, and tranquilizers; therefore, such agents should be avoided or administered in reduced dosage to patients receiving promethazine HCl. When given concomitantly with promethazine, the dose of barbiturates should be reduced by at least one-half, and the dose of narcotics should be reduced by one-quarter to one-half. Dosage must be individualized. Excessive amounts of promethazine HCl relative to a narcotic may lead to restlessness and motor hyperactivity in the patient with pain; these symptoms usually disappear with adequate control of the pain.

Epinephrine – Because of the potential for promethazine to reverse epinephrine’s vasopressor effect, epinephrine should NOT be used to treat hypotension associated with promethazine overdose.

Anticholinergics – Concomitant use of other agents with anticholinergic properties should be undertaken with caution.

Monoamine oxidase inhibitors (MAOI) – Drug interactions, including an increased incidence of extrapyramidal effects, have been reported when some MAOI and phenothiazines are used concomitantly.

Drug/Laboratory Test Interactions

Because narcotic analgesics may increase biliary tract pressure with resultant increases in plasma amylase or lipase levels, determination of these enzyme levels may be unreliable for 24 hours after a narcotic analgesic has been given

The following laboratory tests may be affected in patients who are receiving therapy with promethazine hydrochloride.

Pregnancy Tests: Diagnostic pregnancy tests based on immunological reactions between HCG and anti-HCG may result in false-negative or false-positive interpretations.

Glucose Tolerance Test: An increase in blood glucose has been reported in patients receiving promethazine.

Carcinogenesis, Mutagenesis, Impairment of Fertility

Long-term animal studies have not been performed to assess the carcinogenic potential of codeine or of promethazine, nor are there other animal or human data concerning carcinogenicity, mutagenicity, or impairment of fertility with these agents. Codeine has been reported to show no evidence of carcinogenicity or mutagenicity in a variety of test systems, including the micronucleus and sperm abnormality assays and the Salmonella assay. Promethazine was nonmutagenic in the Salmonella test system of Ames.

Pregnancy

Teratogenic Effects – Pregnancy Category C

Codeine: A study in rats and rabbits reported no teratogenic effect of codeine administered during the period of organogenesis in doses ranging from 5 to 120 mg/kg. In the rat, doses at the 120mg/ kg level, in the toxic range for the adult animal, were associated with an increase in embryo resorption at the time of implantation. In another study a single 100-mg/ kg dose of codeine administered to pregnant mice reportedly resulted in delayed ossification in the offspring.

There are no studies in humans, and the significance of these findings to humans, if any, is not known.

Promethazine: Teratogenic effects have not been demonstrated in ratfeeding studies at doses of 6.25 and 12.5 mg/kg of promethazine HCl. These doses are from approximately 2.1 to 4.2 times the maximum recommended total daily dose of promethazine for a 50kg subject, depending upon the indication for which the drug is prescribed. Daily doses of 25 mg/kg intraperitoneally have been found to produce fetal mortality in rats.

Specific studies to test the action of the drug on parturition, lactation, and development of the animal neonate were not done, but a general preliminary study in rats indicated no effect on these parameters. Although antihistamines have been found to produce fetal mortality in rodents, the pharmacological effects of histamine in the rodent do not parallel those in man. There are no adequate and wellcontrolled studies of promethazine in pregnant women.

Promethazine and codeine should be used during pregnancy only if the potential benefit justifies the potential risk to the fetus.

Nonteratogenic Effects: Dependence has been reported in newborns whose mothers took opiates regularly during pregnancy. Withdrawal signs include irritability, excessive crying, tremors, hyperreflexia, fever, vomiting, and diarrhea. Signs usually appear during the first few days of life.

Promethazine administered to a pregnant woman within two weeks of delivery may inhibit platelet aggregation in the newborn.

Labor and Delivery

Narcotic analgesics cross the placental barrier. The closer to delivery and the larger the dose used, the greater the possibility of respiratory depression in the newborn. Narcotic analgesics should be avoided during labor if delivery of a premature infant is anticipated. If the mother has received narcotic analgesics during labor, newborn infants should be observed closely for signs of respiratory depression. Resuscitation may be required (see OVERDOSAGE).

Limited data suggest that use of promethazine hydrochloride during labor and delivery does not have an appreciable effect on the duration of labor or delivery and does not increase the risk of need for intervention in the newborn.

The effect of promethazine and/or codeine on later growth and development of the newborn is unknown.

Nursing Mothers

It is not known whether promethazine is excreted in human milk.

Codeine is secreted into human milk. In women with normal codeine metabolism (normal CYP2D6 activity), the amount of codeine secreted into human milk is low and dose-dependent. Despite the common use of codeine products to manage postpartum pain, reports of adverse events in infants are rare. However, some women are ultra-rapid metabolizers of codeine. These women achieve higher-than-expected serum levels of codeine’s active metabolite, morphine, leading to higher-than-expected levels of morphine in breast milk and potentially dangerously high serum morphine levels in their breastfed infants. Therefore, maternal use of codeine can potentially lead to serious adverse reactions, including death, in nursing infants.

The risk of infant exposure to codeine and morphine through breast milk should be weighed against the benefits of breastfeeding for both the mother and baby. Caution should be exercised when codeine is administered to a nursing woman. If a codeine containing product is selected, the lowest dose should be prescribed for the shortest period of time to achieve the desired clinical effect. Mothers using codeine should be informed about when to receive immediate medical care and how to identify the signs and symptoms of neonatal toxicity, such as drowsiness or sedation, difficulty breastfeeding, breathing difficulties, and decreased tone, in their baby. Nursing mothers who are ultra-rapid metabolizers may also experience overdose symptoms such as extreme sleepiness, confusion or shallow breathing. Prescribers should closely monitor mother-infant pairs and notify treating pediatricians about the use of codeine during breastfeeding. (See WARNINGS - Death Related to Ultra-Rapid Metabolism of Codeine to Morphine) .

Caution should be exercised when Promethazine Hydrochloride and Codeine Phosphate Syrup is administered to a nursing woman.

Pediatric Use

THE COMBINATION OF PROMETHAZINE HYDROCHLORIDE AND CODEINE PHOSPHATE IS CONTRAINDICATED IN PEDIATRIC PATIENTS LESS THAN 6 YEARS OF AGE, BECAUSE THE COMBINATION MAY CAUSE FATAL RESPIRATORY DEPRESSION IN THIS AGE POPULATION (see WARNINGS – Boxed Warning and Use in Pediatric Patients).

Respiratory depression and death have occurred in children with obstructive sleep apnea who received codeine in the post-operative period following tonsillectomy and/or adenoidectomy and had evidence of being ultra-rapid metabolizers of codeine (i.e., multiple copies of the gene for cytochrome P450 isoenzyme CYP2D6 or high morphine concentrations). These children may be particularly sensitive to the respiratory depressant effects of codeine that has been rapidly metabolized to morphine. Codeine is contraindicated for post-operative pain management in these patients (see WARNINGS – Death Related to Ultra-Rapid Metabolism of Codeine to Morphine and CONTRAINDICATIONS).

The combination of promethazine hydrochloride and codeine phosphate should be used with caution in pediatric patients 6 years and older (see WARNINGS - Use in Pediatric Patients).

Geriatric Use

Clinical studies of Promethazine Hydrochloride and Codeine Phosphate Syrup did not include sufficient numbers of subjects aged 65 and over to determine whether they respond differently from younger subjects. Other reported clinical experience has not identified differences in responses between the elderly and younger patients. In general, dose selection for an elderly patient should be cautious, usually starting at the low end of the dosing range, reflecting the greater frequency of decreased hepatic, renal or cardiac function, and of concomitant disease or other drug therapy.

Sedating drugs may cause confusion and over-sedation in the elderly; elderly patients generally should be started on low doses of Promethazine Hydrochloride and Codeine Phosphate Syrup and observed closely.

ADVERSE REACTIONS

To report SUSPECTED ADVERSE REACTIONS, contact Hi-Tech Pharmacal Co., Inc. at 1-800-262-9010 or FDA at 1-800-FDA-1088 or www.fda.gov/medwatch.

Codeine:

Nervous System - CNS depression, particularly respiratory depression, and to a lesser extent circulatory depression; light-headedness, dizziness, sedation, euphoria, dysphoria, headache, transient hallucination, disorientation, visual disturbances, and convulsions.

Cardiovascular – Tachycardia, bradycardia, palpitation, faintness, syncope, orthostatic hypotension (common to narcotic analgesics).

Gastrointestinal – Nausea, vomiting, constipation, and biliary tract spasm. Patients with chronic ulcerative colitis may experience increased colonic motility; in patients with acute ulcerative colitis, toxic dilation has been reported.

Genitourinary – Oliguria, urinary retention; antidiuretic effect has been reported (common to narcotic analgesics).

Allergic – Infrequent pruritus, giant urticaria, angioneurotic edema, and laryngeal edema.

Other – Flushing of the face, sweating and pruritus (due to opiate-induced histamine release); weakness.

Promethazine:

Central Nervous System - Drowsiness is the most prominent CNS effect of this drug. Sedation, somnolence, blurred vision, dizziness; confusion, disorientation, and extrapyramidal symptoms such as oculogyric crisis, torticollis, and tongue protrusion; lassitude, tinnitus, incoordination, fatigue, euphoria, nervousness, diplopia, insomnia, tremors, convulsive seizures, excitation, catatonic-like states, hysteria. Hallucinations have also been reported.

Cardiovascular – Increased or decreased blood pressure, tachycardia, bradycardia, faintness.

Dermatologic – Dermatitis, photosensitivity, urticaria.

Hematologic – Leukopenia, thrombocytopenia, thrombocytopenic purpura, agranulocytosis.

Gastrointestinal - Dry mouth, nausea, vomiting, jaundice.

Respiratory - Asthma, nasal stuffiness, respiratory depression (potentially fatal) and apnea (potentially fatal). (See WARNINGS-Promethazine; Respiratory Depression.)

Other-Angioneurotic edema. Neuroleptic malignant syndrome (potentially fatal) has also been reported. (See WARNINGS-Promethazine; Neuroleptic Malignant Syndrome.)

Paradoxical Reactions- Hyperexcitability and abnormal movements have been reported in patients following a single administration of promethazine HCl. Consideration should be given to the discontinuation of promethazine HCl and to the use of other drugs if these reactions occur. Respiratory depression, nightmares, delirium, and agitated behavior have also been reported in some of these patients.

DRUG ABUSE AND DEPENDENCE

Controlled Substance

Promethazine hydrochloride and codeine phosphate syrup is a Schedule V Controlled Substance.

Abuse

Codeine is known to be subject to abuse; however, the abuse potential of oral codeine appears to be quite low. Even parenteral codeine does not appear to offer the psychic effects sought by addicts to the same degree as heroin or morphine. However, codeine must be administered only under close supervision to patients with a history of drug abuse or dependence

Dependence

Psychological dependence, physical dependence, and tolerance are known to occur with codeine.

OVERDOSAGE

Codeine: Serious overdose with codeine is characterized by respiratory depression (a decrease in respiratory rate and/or tidal volume, Cheyne-Stokes respiration, cyanosis), extreme somnolence progressing to stupor or coma, skeletal muscle flaccidity, cold and clammy skin, and sometimes bradycardia and hypotension. The triad of coma, pinpoint pupils, and respiratory depression is strongly suggestive of opiate poisoning. In severe overdosage, particularly by the intravenous route, apnea, circulatory collapse, cardiac arrest, and death may occur. Promethazine is additive to the depressant effects of codeine. It is difficult to determine what constitutes a standard toxic or lethal dose. However, the lethal oral dose of codeine in an adult is reported to be in the range of 0.5 to 1.0 gram. Infants and children are believed to be relatively more sensitive to opiates on a body-weight basis. Elderly patients are also comparatively intolerant to opiates.

Promethazine: Signs and symptoms of overdosage with promethazine HCl range from mild depression of the central nervous system and cardiovascular system to profound hypotension, respiratory depression, unconsciousness, and sudden death. Other reported reactions include hyperreflexia, hypertonia, ataxia, athetosis, and extensor-plantar reflexes (Babinski reflex).

Stimulation may be evident, especially in children and geriatric patients. Convulsions may rarely occur. A paradoxical-type reaction has been reported in children receiving single doses of 75 mg to 125 mg orally, characterized by hyperexcitability and nightmares.

Atropine-like signs and symptoms – dry mouth, fixed dilated pupils, flushing, as well as gastrointestinal symptoms may occur.

Treatment: The treatment of overdosage with promethazine and codeine is essentially symptomatic and supportive. Only in cases of extreme overdosage or individual sensitivity do vital signs including respiration, pulse, blood pressure, temperature, and EKG need to be monitored.

Activated charcoal orally or by lavage may be given, or sodium or magnesium sulfate orally as a cathartic. Attention should be given to the reestablishment of adequate respiratory exchange through provision of a patent airway and institution of assisted or controlled ventilation. The narcotic antagonist, naloxone hydrochloride, may be administered when significant respiratory depression occurs with promethazine and codeine; any depressant effects of promethazine are not reversed with naloxone. Diazepam may be used to control convulsions. Avoid analeptics, which may cause convulsions. Acidosis and electrolyte losses should be corrected. A rise in temperature or pulmonary complications may signal the need for institution of antibiotic therapy.

Severe hypotension usually responds to the administration of norepinephrine or phenylephrine. EPINEPHRINE SHOULD NOT BE USED, since its use in a patient with partial adrenergic blockade may further lower the blood pressure.

Limited experience with dialysis indicates that it is not helpful.

DOSAGE AND ADMINISTRATION

The combination of promethazine hydrochloride and codeine phosphate is contraindicated in pediatric patients less than 6 years of age, because the combination may cause fatal respiratory depression in this age population.

It is important that Promethazine Hydrochloride and Codeine Phosphate Syrup is measured with an accurate measuring device (see PRECAUTIONS- Information for Patients). A household teaspoon is not an accurate measuring device and could lead to overdosage, especially when a half a teaspoon is to be measured. It is strongly recommended that an accurate measuring device be used. A pharmacist can provide an appropriate measuring device and can provide instructions for measuring the correct dose.

The average effective dose for adults and children 12 years and over is: 1 teaspoonful (5 mL) every 4 to 6 hours, not to exceed 30 mL in 24 hours.

The average effective dose for children 6 years to under 12 years of age is: ½ to 1 teaspoonful (2.5 to 5 mL) every 4 to 6 hours, not to exceed 30 mL in 24 hours.

HOW SUPPLIED

Promethazine Hydrochloride and Codeine Phosphate Syrup contains promethazine hydrochloride 6.25 mg/5 mL, codeine phosphate 10 mg/5 mL and alcohol 7 percent. It is supplied as follows:

NDC 12634-909-02 60 mL Bottle

NDC 12634-909-04 120mL Bottle

NDC 12634-909-06 178mL Bottle

NDC 12634-909-08 237 mL Bottle

NDC 12634-909-16 473 mL Bottle

NDC 12634-909-28 3785 mL Bottle

NDC 12634-909-32 946 mL Bottle

Store at 20° - 25°C (68° - 77°F) [see USP Controlled Room Temperature].

Dispense in a tight, light-resistant container as defined in the USP.

Manufactured by

Hi-Tech Pharmacal Co., Inc.

Amityville, NY 11701

Rev. 804:08 05/15

Repackged and Distributed by:

Apotheca Inc.

Phoenix, AZ 85006

PRINCIPAL DISPLAY PANEL

PROMETHAZINE HYDROCHLORIDE AND CODEINE PHOSPHATE SYRUP

6.25 mg/10 mg per 5 mL

Each 5 mL contains:

Promethazine Hydrochloride ……………. 6.25 mg

Codeine Phosphate ………………………….10 mg

Alcohol ………………………………………..7%

Contains FD&C Yellow No. 6

USUAL DOSAGE: See attached insert for full prescribing information.

Keep tightly closed. Store at room temperature between 20° and 25°C (68° and 77°F). [See USP Controlled Room Temperature]. Protect from light. Dispense in a tight, light-resistant container, as defined in the USP.